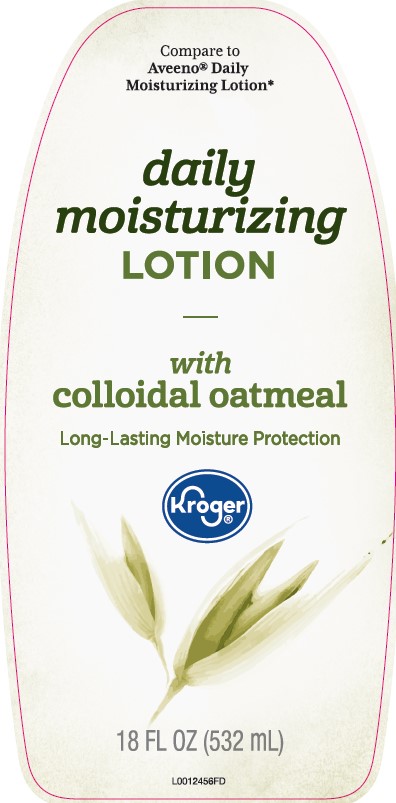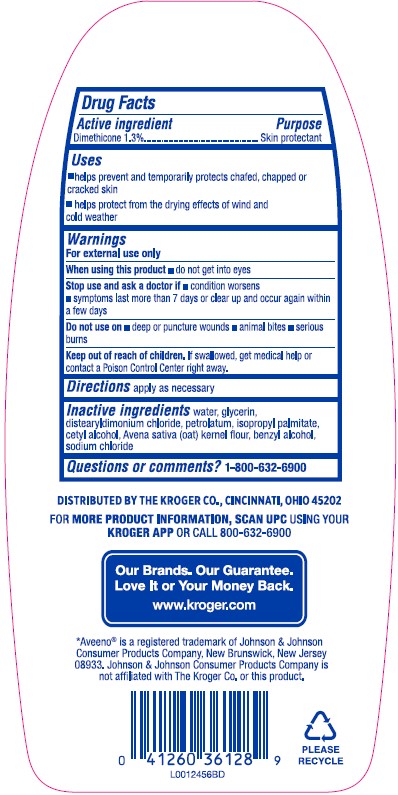 DRUG LABEL: Daily Moisturizing
NDC: 30142-619 | Form: LOTION
Manufacturer: The Kroger Co.
Category: otc | Type: HUMAN OTC DRUG LABEL
Date: 20260227

ACTIVE INGREDIENTS: DIMETHICONE 13 mg/1 mL
INACTIVE INGREDIENTS: WATER; GLYCERIN; DISTEARYLDIMONIUM CHLORIDE; PETROLATUM; ISOPROPYL PALMITATE; CETYL ALCOHOL; OATMEAL; BENZYL ALCOHOL; SODIUM CHLORIDE

Kroger 619.003-619AC rev 2
Daily Moisturizing Lotion

Active ingredient

Dimethicone 1.3%

Purpose

Skin Protectant

Uses

- helps prevent and temporarily protects chafed, chapped or cracked skin
- helps protect from the drying effects of wind and cold weather

Warnings

For external use only

When using this product

- do not get into eyes

Stop use and ask a doctor if

- conditions worsens
- symptoms last more than 7 days or clear up and occur again within a few days

Do not use

- on deep or puncture wounds
- animal bites
- serious burns

Keep out of reach of children.

If swallowed, get medical help or contact a Poison Control Center right away.

Directions

apply as necessary

Inactive ingredients

water, glycerin, distearyldimonium chloride, petrolatum, isopropyl palmitate, cetyl alcohol, Avena sativa (oat) kernel flour, benzyl alcohol, sodium chloride

Questions or comments?

1-800-632-6900

ADVERSE REACTION

DISTRIBUTED BY THE KROGER CO., CINCINNATI, OHIO 45202

FOR MORE PRODUCT INFORMATION, SCAN UPC USING YOUR KROGER APP OR CALL 800-632-6900

Our brands. Our Guarantee.

Love It or Your Money Back.

www.kroger.com

*Aveeno®is a registered trademark of Johnson & Johnson Consumer Product Company, New Brunswick, New Jersey 08933.

Johnson & Johnson Consumer Product Company is not affiliated with The Kroger Co. or this product.

PLEASE RECYCLE

principal display panel

Compare to Aveeno® Daily Moisturizing Lotion*

daily moisturizing Lotion

with colloidal oatmeal

Long-Lasting Moisture Protection

Kroger®

18 FL OZ (532 mL)